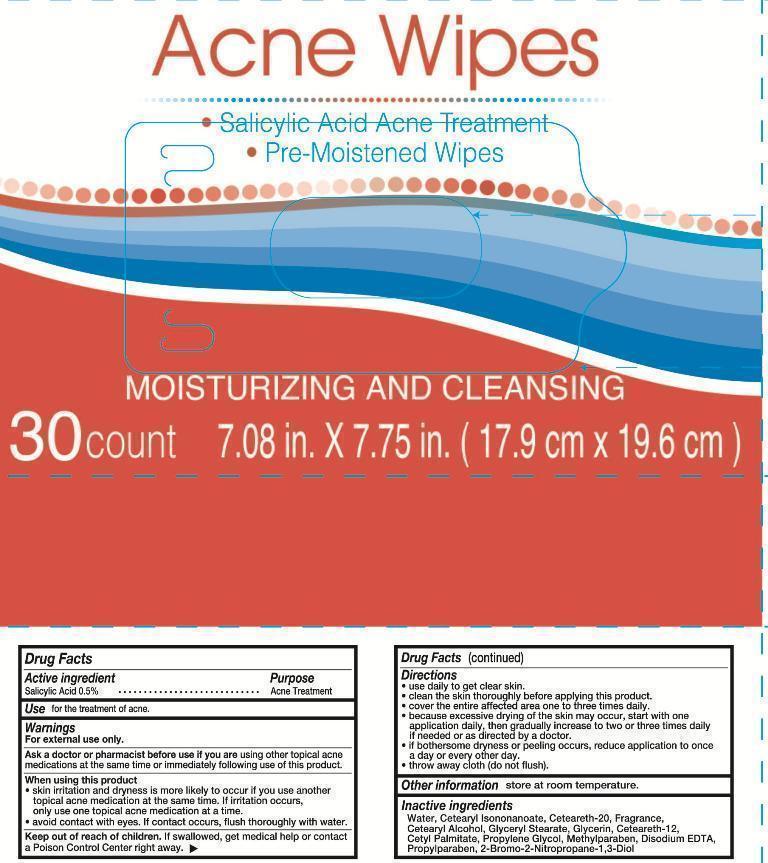 DRUG LABEL: Acne wipes
NDC: 42255-603 | Form: SWAB
Manufacturer: ZHEJIANG GREENFACE HOUSEWARES CO., LTD.
Category: otc | Type: HUMAN OTC DRUG LABEL
Date: 20180108

ACTIVE INGREDIENTS: SALICYLIC ACID 0.5 g/100 g
INACTIVE INGREDIENTS: CETEARYL ISONONANOATE; CETEARETH-2 PHOSPHATE; CETYL ACETATE; GLYCERYL STEARATE CITRATE; GLYCERIN; CETEARETH-12; CETYL PALMITATE; PROPYLENE GLYCOL; METHYLPARABEN; DISODIUM EDTA-COPPER; PROPYLPARABEN; 2-BROMO-2-NITROETHANOL; WATER

Acne wipes 30ct 603

Active ingredient

salicylic acid 0.5%

Purpose

Acne treatment

Uses

For the treatment oa acne

Warnings

For external use only.

Ask a doctor or pharmecist before use if you are using other topical acne medications at the same time or immediately following use of this product.

When using this product

skin irritaiton and dryness is more likely to occur if you use another topical acne medication at the same time.if irritation occurs.

only use one topical acne medication at a time.

avoid contact with eyes,if contact occurs,rlush rhoroughly with water.

Keep out of reach of children

If swallowed, get medical help or contact a Poison Control Center right away.

Directions

use daily to get clear skin.

clean the skin thoroughly before applying this product.

cover the entire affected area one to three times daily.

because excessive drying of te skin may occur ,start with one application daily ,then gradually increase to two or three times daily if needed or as directed by a doctor.

if bothersome dryness or peeling occurs,reduce application to once a day or every other day.

throw away cloth (do not flush)

store at room temperture.

INACTIVE INGREDIENT

Water, salicylic acid,Cetearyl isononanoate,Ceteareth-20,fragrance,Cetearyl alcohol,Glyceryl stearate,glycerin,Ceteareth-12,Cetyl palmitate,Propylene glycol,methylparaben,Disodium EDTA,Propylparaben,2-bromo-2-nitropropane-1,3-diol